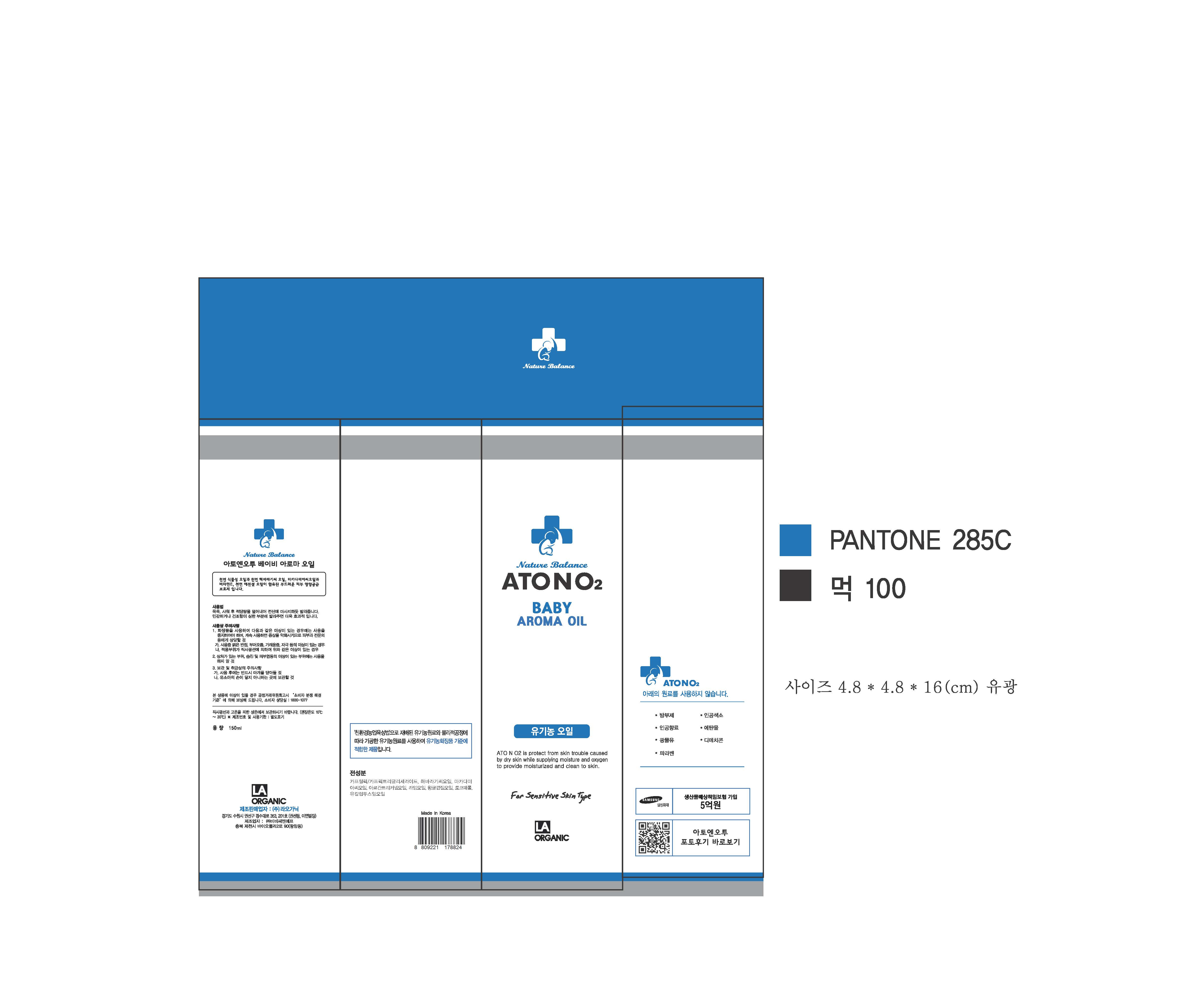 DRUG LABEL: ATONO2 BABY AROMA
NDC: 70993-0002 | Form: OIL
Manufacturer: LAORGANIC Co., Ltd.
Category: otc | Type: HUMAN OTC DRUG LABEL
Date: 20161012

ACTIVE INGREDIENTS: SUNFLOWER OIL 14 g/100 mL; MACADAMIA OIL 11 g/100 mL
INACTIVE INGREDIENTS: TOCOPHEROL

Drug Facts

ACTIVE INGREDIENT

Helianthus Annuus (Sunflower) Seed Oil, Macadamia Ternifolia seed Oil

INACTIVE INGREDIENT

Caprylic/Capric Triglyceride, Argania Spinosa Kernel Oil, Citrus Aurantifolia (Lime) Oil, Citrus Grandis (Grapefruit) Peel Oil, Tocopherol

PURPOSE

Skin Protectant

keep out of reach of the children

INDICATIONS AND USAGE

Apply proper amount to the skin.

WARNINGS

- For external use only
- When using this product

1. If any one of following symptoms occurs when using cosmetics, stop using it and consult a dermatologist.
A. red spot, swelling, itching, stimulus
B. symptoms mentioned above are caused by sunlight.

2. Do not apply on skin where there is wound, eczema, or irritation.

3. Storage and cautions for handling
A. Close stopper after using.
B. Keep out of reach of children.
C. Keep away from high or low temperature and direct sunlight.

4. This is not a medicinal product. Made of 100% cosmetic ingredients, it is a sensitive-skin care product for all skin types.

DOSAGE AND ADMINISTRATION

for external use only